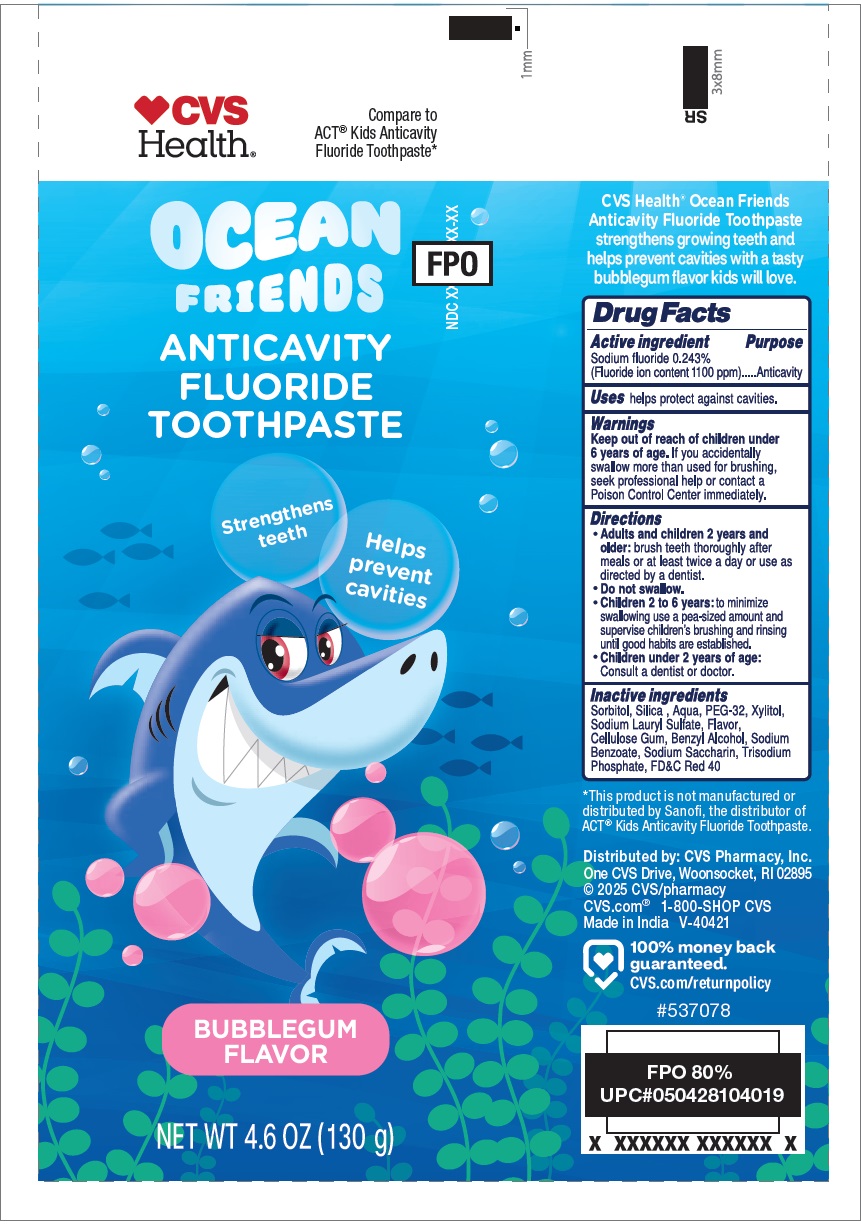 DRUG LABEL: OCEAN FRIENDS ANTICAVITY FLUORIDE BUBBLEGUM FLAVOR
NDC: 51316-163 | Form: PASTE, DENTIFRICE
Manufacturer: CVS Pharmacy, Inc.
Category: otc | Type: HUMAN OTC DRUG LABEL
Date: 20241017

ACTIVE INGREDIENTS: SODIUM FLUORIDE 0.243 g/100 g
INACTIVE INGREDIENTS: SORBITOL; SILICON DIOXIDE; WATER; POLYETHYLENE GLYCOL 1600; XYLITOL; SODIUM LAURYL SULFATE; CARBOXYMETHYLCELLULOSE SODIUM, UNSPECIFIED; BENZYL ALCOHOL; SODIUM BENZOATE; SACCHARIN SODIUM; SODIUM PHOSPHATE, TRIBASIC, ANHYDROUS; FD&C RED NO. 40

OCEAN FRIENDS ANTICAVITY FLUORIDE TOOTHPASTE BUBBLEGUM FLAVOR

Active ingredient

Sodium fluoride 0.243%
(Fluoride ion content 1100 ppm)

Purpose

Anticavity

Uses

helps protect against cavities.

Warnings

Keep out of reach of children under 6 years of age. If you accidentally swallow more than used for brushing, seek professional help or contact a Poison Control Center immediately.

Directions

• Adults and children 2 years and older: brush teeth thoroughly after meals or at least twice a day or use as directed by a dentist.
• Do not swallow.
• Children 2 to 6 years: to minimize swallowing use a pea-sized amount and supervise children's brushing and rinsing until good habits are established.
• Children under 2 years of age: Consult a dentist or doctor.

Inactive ingredients

Sorbitol, Silica, Aqua, PEG-32, Xylitol, Sodium Lauryl Sulfate, Flavor, Cellulose Gum, Benzyl Alcohol, Sodium Benzoate, Sodium Saccharin, Trisodium Phosphate, FD&C Red 40

Compare to ACT® Kids Anticavity Fluoride Toothpaste*

Strengthens teeth

Helps prevent cavities

CVS Health® Ocean Friends Anticavity Fluoride Toothpaste strengthens growing teeth and helps prevent cavities with a tasty bubblegum flavor kids will love.

*This product is not manufactured or distributed by Sanofi, the distributor of ACT® Kids Anticavity Fluoride Toothpaste.

Distributed by: CVS Pharmacy, Inc.
One CVS Drive, Woonsocket, RI 02895
©2025 CVS/pharmacy
CVS.com® 1-800-SHOP CVS
Made in India V-40421

100% money back guaranteed.
CVS.com/returnpolicy